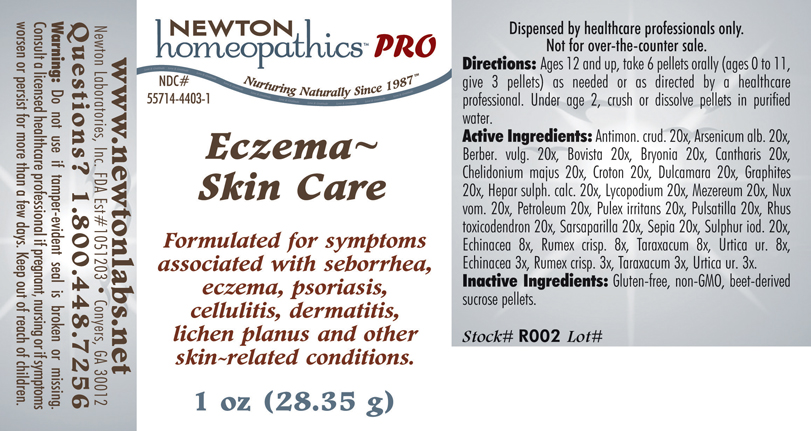 DRUG LABEL: Eczema Skin Care 
NDC: 55714-4403 | Form: PELLET
Manufacturer: Newton Laboratories, Inc.
Category: homeopathic | Type: HUMAN PRESCRIPTION DRUG LABEL
Date: 20110601

ACTIVE INGREDIENTS: Antimony Trisulfide 20 [hp_X]/1 g; Arsenic Trioxide 20 [hp_X]/1 g; Berberis Vulgaris Root Bark 20 [hp_X]/1 g; Giant Puffball 20 [hp_X]/1 g; Bryonia Alba Root 20 [hp_X]/1 g; Lytta Vesicatoria 20 [hp_X]/1 g; Chelidonium Majus 20 [hp_X]/1 g; Croton Tiglium Seed 20 [hp_X]/1 g; Solanum Dulcamara Top 20 [hp_X]/1 g; Graphite 20 [hp_X]/1 g; Calcium Sulfide 20 [hp_X]/1 g; Lycopodium Clavatum Spore 20 [hp_X]/1 g; Daphne Mezereum Bark 20 [hp_X]/1 g; Strychnos Nux-vomica Seed 20 [hp_X]/1 g; Kerosene 20 [hp_X]/1 g; Pulex Irritans 20 [hp_X]/1 g; Pulsatilla Vulgaris 20 [hp_X]/1 g; Toxicodendron Pubescens Leaf 20 [hp_X]/1 g; Smilax Regelii Root 20 [hp_X]/1 g; Sepia Officinalis Juice 20 [hp_X]/1 g; Sulfur Iodide 20 [hp_X]/1 g; Echinacea, Unspecified 8 [hp_X]/1 g; Rumex Crispus Root 8 [hp_X]/1 g; Taraxacum Officinale 8 [hp_X]/1 g; Urtica Urens 8 [hp_X]/1 g
INACTIVE INGREDIENTS: Sucrose

Eczema Skin Care

INDICATIONS & USAGE SECTION

ECZEMA~SKIN CARE Formulated for symptoms associated with seborrhea, eczema, psoriasis, cellulitis, dermatitis, lichen planus and other skin-related conditions.

DOSAGE & ADMINISTRATION SECTION

Directions: Ages 12 and up, take 6 pellets orally (ages 0 to 11, give 3 pellets) as needed or as directed by a healthcare professional. Under age 2, crush or dissolve pellets in purified water.

ACTIVE INGREDIENT SECTION

Antimon. crud. 20x, Arsenicum alb. 20x, Berber. vulg. 20x, Bovista 20x, Bryonia 20x, Cantharis 20x, Chelidonium majus 20x, Croton 20x, Dulcamara 20x, Graphites 20x, Hepar sulph. calc. 20x, Lycopodium 20x, Mezereum 20x, Nux vom. 20x, Petroleum 20x, Pulex irritans 20x, Pulsatilla 20x, Rhus toxicodendron 20x, Sarsaparilla 20x, Sepia 20x, Sulphur iod. 20x, Echinacea 8x, Rumex crisp. 8x, Taraxacum 8x, Urtica ur. 8x, Echinacea 3x, Rumex crisp. 3x, Taraxacum 3x, Urtica ur. 3x.

INACTIVE INGREDIENT SECTION

Inactive Ingredients: Gluten-free, non-GMO, beet-derived sucrose pellets.

QUESTIONS? SECTION

www.newtonlabs.net Newton Laboratories, Inc. FDA Est # 1051203 - Conyers, GA 30012
Questions? 1.800.448.7256

WARNINGS SECTION

Warning: Do not use if tamper- evident seal is broken or missing. Consult a licensed healthcare professional if pregnant, nursing or if symptoms worsen or persist for more than a few days. Keep out of reach of children.

PREGNANCY OR BREAST FEEDING SECTION

Consult a licensed healthcare professional if pregnant, nursing or if symptoms worsen or persist for more than a few days.

KEEP OUT OF REACH OF CHILDREN SECTION

Keep out of reach of children.